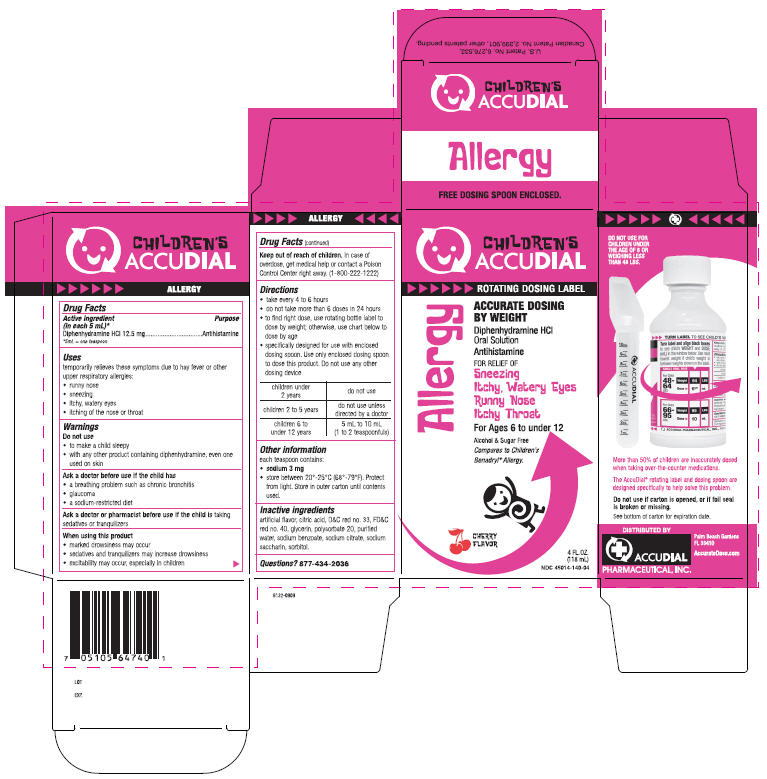 DRUG LABEL: Allergy
NDC: 45014-140 | Form: LIQUID
Manufacturer: Accudial Pharmaceutical, Inc.
Category: otc | Type: HUMAN OTC DRUG LABEL
Date: 20091102

ACTIVE INGREDIENTS: Diphenhydramine Hydrochloride 12.5 mg/5 mL
INACTIVE INGREDIENTS: Citric Acid Monohydrate; D&C RED NO. 33; FD&C RED NO. 40; Glycerin; Polysorbate 20; Water; Sodium Benzoate; Sodium Citrate; Saccharin Sodium; Sorbitol

CHILDREN'S
ACCUDIAL

ALLERGY

Drug Facts

Active ingredient (in each 5 mL) [5mL = one teaspoon]

Diphenhydramine HCl 12.5 mg

Purpose

Antihistamine

Uses

temporarily relieves these symptoms due to hay fever or other upper respiratory allergies:

- runny nose
- sneezing
- itchy, watery eyes
- itching of the nose or throat

Warnings

Do not use

- to make a child sleepy
- with any other product containing diphenhydramine, even one used on skin

Ask a doctor before use if the child has

- a breathing problem such as chronic bronchitis
- glaucoma
- a sodium-restricted diet

Ask a doctor or pharmacist before use if the child is taking sedatives or tranquilizers

When using this product

- marked drowsiness may occur
- sedatives and tranquilizers may increase drowsiness
- excitability may occur, especially in children

Keep out of reach of children. In case of overdose, get medical help or contact a Poison Control Center right away. (1-800-222-1222)

Directions

- take every 4 to 6 hours
- do not take more than 6 doses in 24 hours
- to find right dose, use rotating bottle label to dose by weight; otherwise, use chart below to dose by age
- specifically designed for use with enclosed dosing spoon. Use only enclosed dosing spoon to dose this product. Do not use any other dosing device

children under 2 years | do not use
children 2 to 5 years | do not use unless directed by a doctor
children 6 to under 12 years | 5 mL to 10 mL (1 to 2 teaspoonfuls)

Other information

each teaspoon contains:

- sodium 3 mg
- store between 20°-25°C (68°-79°F). Protect from light. Store in outer carton until contents used.

Inactive ingredients

artificial flavor, citric acid, D&C red no. 33, FD&C red no. 40, glycerin, polysorbate 20, purified water, sodium benzoate, sodium citrate, sodium saccharin, sorbitol.

Questions?

877-434-2036

PRINCIPAL DISPLAY PANEL - 118 mL Carton

CHILDREN'S
ACCUDIAL

ROTATING DOSING LABEL

ACCURATE DOSING
BY WEIGHT

Diphenhydramine HCl
Oral Solution
Anthistamine

FOR RELIEF OF
Sneezing
Itchy, Watery Eyes
Runny Nose
Itchy Throat

For Ages 6 to under 12

Alcohol & Sugar Free
Compares to Children's
Benadryl® Allergy.

CHERRY
FLAVOR

4 FL. OZ.
(118 mL)
NDC 45014-140-04

Allergy